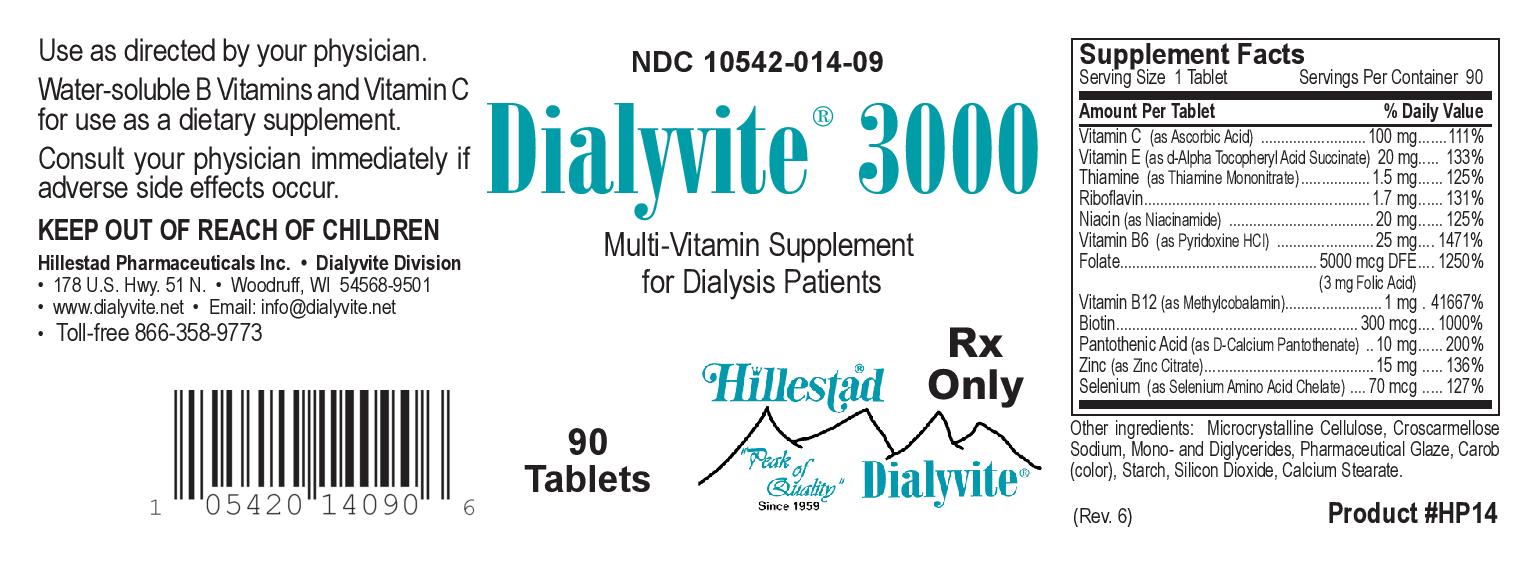 DRUG LABEL: Dialyvite 3000
NDC: 10542-014 | Form: TABLET, COATED
Manufacturer: Hillestad Pharmaceuticals USA
Category: prescription | Type: HUMAN PRESCRIPTION DRUG LABEL
Date: 20270127

ACTIVE INGREDIENTS: Ascorbic Acid 100 mg/1 1; Thiamine Mononitrate 1.5 mg/1 1; Riboflavin 1.7 mg/1 1; Niacinamide 20 mg/1 1; Pyridoxine Hydrochloride 25 mg/1 1; Folic Acid 3 mg/1 1; Cobalamin 1 mg/1 1; Biotin 300 ug/1 1; Calcium Pantothenate 10 mg/1 1; Zinc Citrate 15 mg/1 1; .alpha.-tocopherol succinate, d-  30 [iU]/1 1; Selenocysteine 70 ug/1 1
INACTIVE INGREDIENTS: Microcrystalline Cellulose; Croscarmellose Sodium; Glyceryl Monostearate; Carob; Shellac; Starch, Corn; Calcium Stearate; Silicon Dioxide

Dialyvite 3000

DESCRIPTION

Dialyvite 3000 is a prescription folic acid supplement with additional nutrients for kidney dialysis patients. Dialyvite 3000 is a small, round, light brown, clear-coated tablet, with debossed "H" on one side.

Each tablet contains:

Folic Acid.....3 mg

Vitamin E (d-alpha Tocopheryl Acid Succinate).....30 IU

Vitamin C (Ascorbic Acid).....100 mg

Thiamine (Thiamine Mononitrate).....1.5 mg

Riboflavin.....1.7 mg

Niacinamide.....20 mg

Vitamin B6 (Pyridoxine HCl).....25 mg

Vitamin B12 (Methylcobalamin).....1 mg

Biotin.....300 mcg

Pantothenic Acid (Calcium Pantothenate).....10 mg

Zinc (Zinc Citrate).....15 mg

Selenium (Selenium Amino Acid Chelate).....70 mcg

Inactive ingredients:

Microcrystalline Cellulose, Croscarmellose Sodium, Mono-and Diglycerides, Pharmaceutical Glaze, Carob (color), Starch, Calcium Stearate, Silicon Dioxide.

INDICATIONS AND USAGE

Dialyvite 3000 is a prescription folic acid supplement with additional nutrients indicated for use in improving the nutritional status of renal dialysis patients.

CONTRAINDICATIONS

This product is contraindicated in patients with known hypersensitivity to any of the ingredients.

PRECAUTIONS

Folic acid supplementation may obscure pernicious anemia, in that hematologic remission can occur while neurological manifestations progress.

Keep out of reach of children.

ADVERSE REACTIONS

Allergic sensitizations have been reported following oral administration of folic acid.

Consult your physician immediately if adverse side effects occur.

DOSAGE AND ADMINISTRATION

Take one tablet per day or use as directed by your physician, orally.

PRINCIPAL DISPLAY PANEL

NDC 10542-014-09

Dialyvite 3000

Multivitamin Supplement for Dialysis Patients

90 Tablets